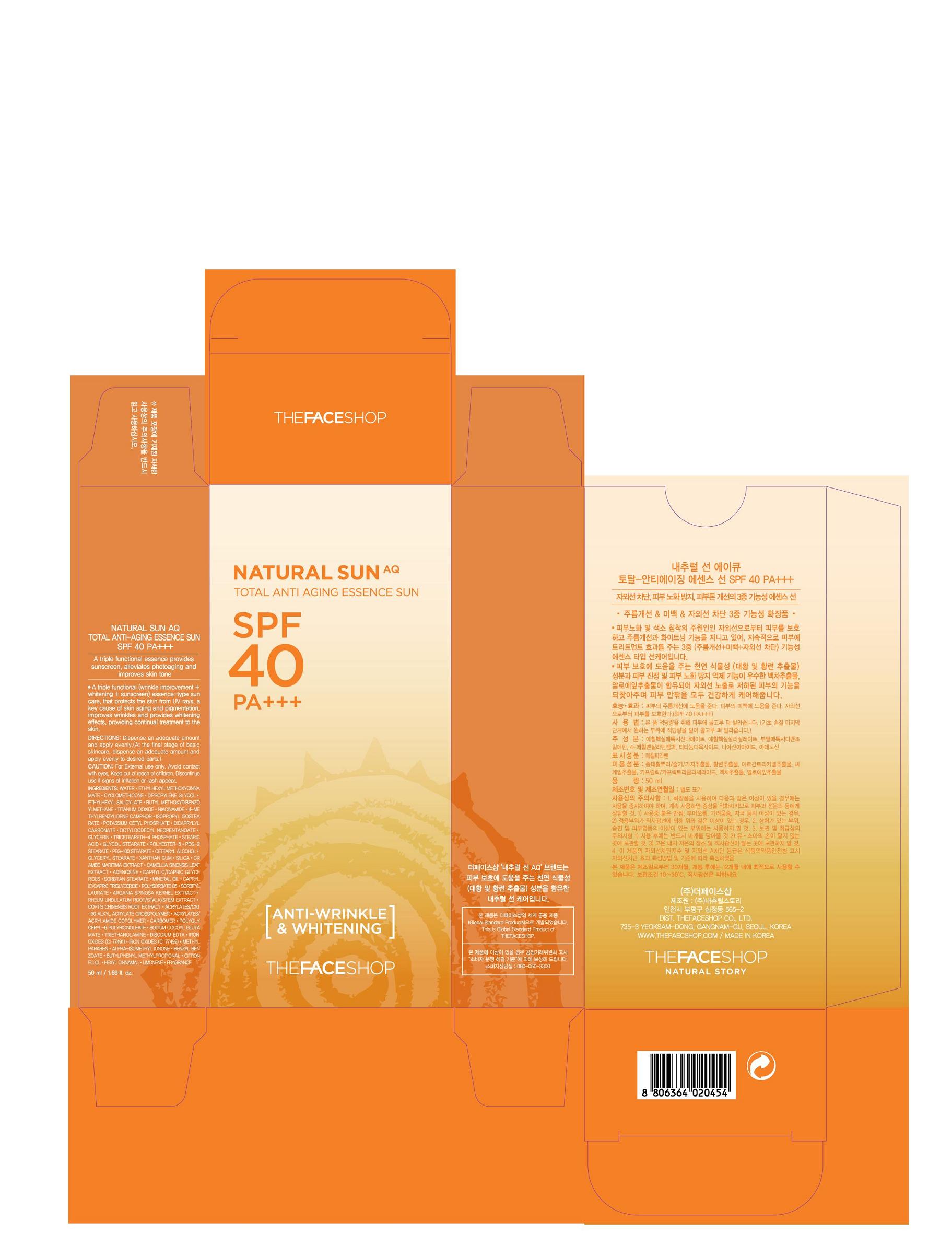 DRUG LABEL:  NATURAL SUN AQ TOTAL ANTI-AGING ESSENCE SUN
NDC: 51523-102 | Form: CREAM
Manufacturer: THEFACESHOP CO., LTD
Category: otc | Type: HUMAN OTC DRUG LABEL
Date: 20101129

ACTIVE INGREDIENTS: OCTINOXATE 7.5 mL/100 mL; OCTISALATE 3 mL/100 mL; TITANIUM DIOXIDE 2.34 mL/100 mL; AVOBENZONE 2.3 mL/100 mL; ENZACAMENE 2 mL/100 mL; NIACINAMIDE 2 mL/100 mL; ADENOSINE 0.4 mL/100 mL
INACTIVE INGREDIENTS: WATER; CYCLOMETHICONE; GLYCERIN; DIPROPYLENE GLYCOL; DICAPRYLYL CARBONATE; OCTYLDODECYL NEOPENTANOATE; POTASSIUM CETYL PHOSPHATE; FERRIC OXIDE RED; FERRIC OXIDE YELLOW; POLYOXYL 100 STEARATE; METHYLPARABEN; CETOSTEARYL ALCOHOL; XANTHAN GUM; STEARIC ACID; EDETATE DISODIUM; BENZYL BENZOATE; BUTYLPHENYL METHYLPROPIONAL; .ALPHA.-HEXYLCINNAMALDEHYDE; TROLAMINE; SILICON DIOXIDE; GLYCERYL MONOSTEARATE; GLYCOL STEARATE; MINERAL OIL

Drug Facts

ACTIVE INGREDIENT

OCTINOXATE (7.50%)
OCTISALATE (3.00%)
TITANIUM DIOXIDE (2.34%)
AVOBENZONE (2.30%)
ENZACAMENE (2.00%)
NIACINAMIDE (2.00%)
ADENOSINE (0.04%)

INACTIVE INGREDIENT

WATER ∙ CYCLOMETHICONE ∙ DIPROPYLENE GLYCOL ∙ POTASSIUM CETYL PHOSPHATE ∙ DICAPRYLYL CARBONATE ∙ OCTYLDODECYL NEOPENTANOATE ∙ GLYCERIN ∙ STEARIC ACID ∙ GLYCOL STEARATE ∙ POLYOXYL 100 STEARATE ∙ CETEARYL ALCOHOL ∙ GLYCERYL STEARATE ∙ XANTHAN GUM ∙ SILICON DIOXIDE ∙ SORBITAN MONOSTEARATE ∙ MINERAL OIL ∙ TROLAMINE ∙ EDETATE DISODIUM ∙ FERRIC OXIDE RED ∙ FERRIC OXIDE YELLOW ∙ METHYLPARABEN ∙ BENZYL BENZOATE ∙ BUTYLPHENYL METHYLPROPIONAL ∙ .ALPHA.-HEXYLCINNAMALDEHYDE

PURPOSE

Anti Aging Essence Sun Block

WHEN USING

Avoid contact with eyes.

STOP USE

Discontinue use if sign of irritation or rash appear.

DOSAGE AND ADMINISTRATION

Dispense an adequate amount and apply evenly. (At the final stage of basic skincare, dispense an adequate amount and apply evenly to desired parts)

PACKAGE LABEL

NATURAL SUN AQ TOTAL ANTI-AGING ESSENCE SUN